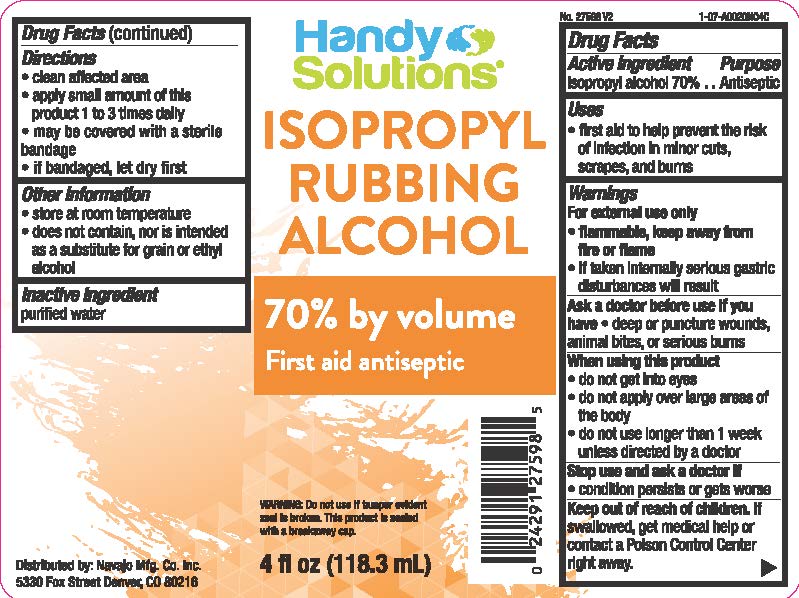 DRUG LABEL: Handy Solutions Rubbing Alcohol
NDC: 67751-002 | Form: LIQUID
Manufacturer: Navajo Manufacturing Company Inc.
Category: otc | Type: HUMAN OTC DRUG LABEL
Date: 20241115

ACTIVE INGREDIENTS: ISOPROPYL ALCOHOL 700 mg/1 mL
INACTIVE INGREDIENTS: WATER

Handy Solutions Rubbing Alcohol

Active ingredient

Isopropyl alcohol 70%

Purpose

First Aid Antiseptic

Uses

- first aid to help prevent the risk of infection in:
  - minor cuts
  - scrapes
  - burns

Warnings

For external use only

Flammable

- keep away from fire or flame, heat, spark, electrical. Flash point 72°F

• do not use

with electrocautery procedures.

Ask a doctor before use if you have

deep or puncture wounds, animal bites or serious burns

When using this product

- do not get into eyes
- do not apply over large areas of the body
- do not use longer than 1 week unless directed by a doctor

Stop use and ask a doctor if

condition persists or gets worse

Keep out of reach of children.

If swallowed, get medical help or contact a Poison Control Center right away.

Directions

- clean the affected area
- apply 1 to 3 times daily

Other information

- does not contain, nor is intended as a substitute for grain or ethyl alcohol
- will produce serious gastric disturbances if taken internally

Inactive ingredient

purified water

Handy Solutions

is a Trademark of Navajo Mfg. Co. Inc
5330 Fox 5t., Denver, CO 80216

PACKAGE LABEL

Handy Solutions ISOPROPYL RUBBING ALCOHOL

70% by volume

First aid antiseptic

Warning: Do not use if tamper evident seal is broken. This product is sealed with a breakaway cap.

4 FL OZ (118 ml)